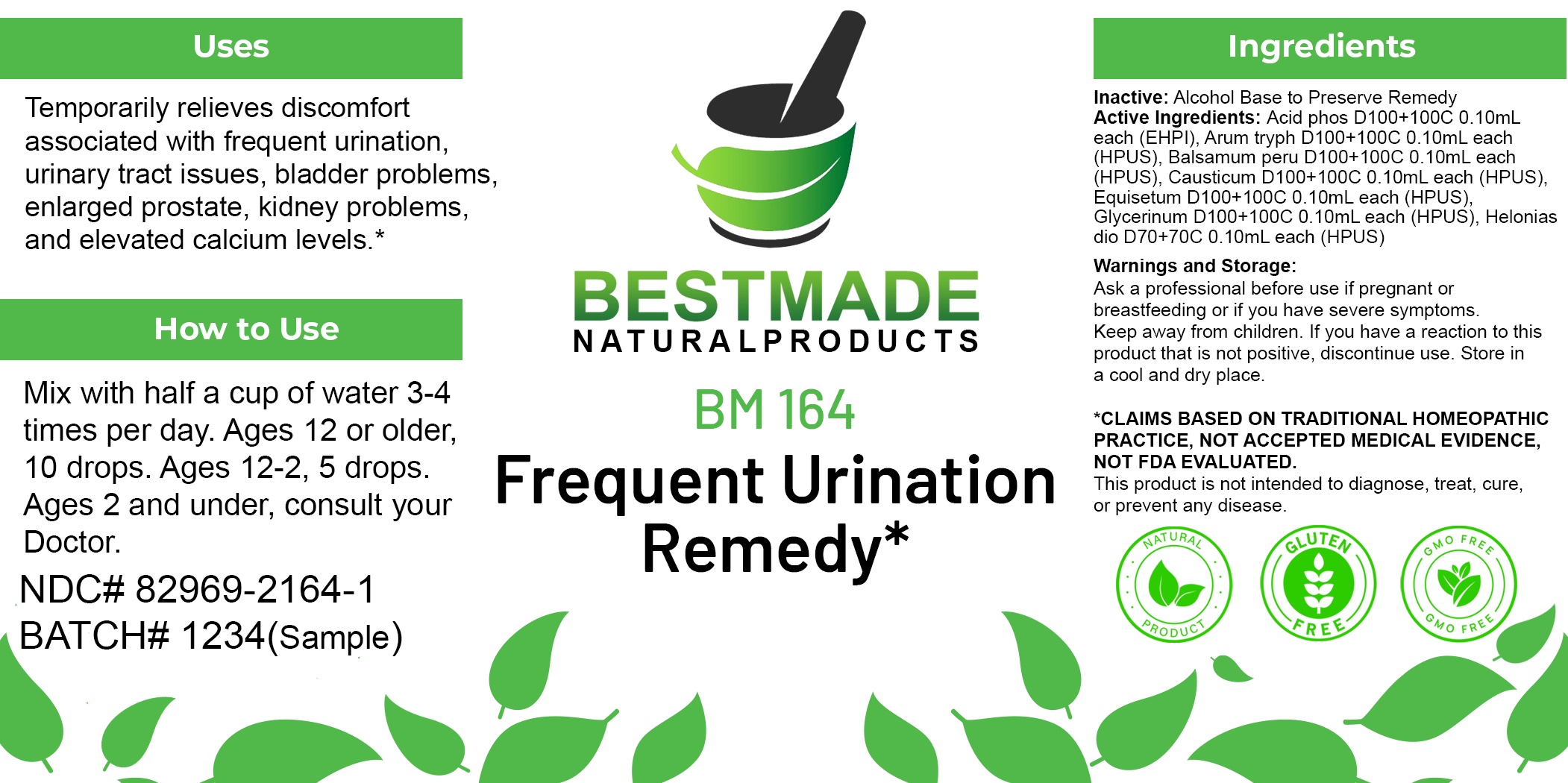 DRUG LABEL: Bestmade Natural Products BM164
NDC: 82969-2164 | Form: LIQUID
Manufacturer: Bestmade Natural Products
Category: homeopathic | Type: HUMAN OTC DRUG LABEL
Date: 20250218

ACTIVE INGREDIENTS: CAUSTICUM 30 [hp_C]/30 [hp_C]; CHAMAELIRIUM LUTEUM ROOT 30 [hp_C]/30 [hp_C]; EQUISETUM HYEMALE WHOLE 30 [hp_C]/30 [hp_C]; ARISAEMA TRIPHYLLUM ROOT 30 [hp_C]/30 [hp_C]; PHOSPHORIC ACID 30 [hp_C]/30 [hp_C]; BALSAM PERU 30 [hp_C]/30 [hp_C]; GLYCERIN 30 [hp_C]/30 [hp_C]
INACTIVE INGREDIENTS: ALCOHOL 30 [hp_C]/30 [hp_C]

BM164

DOSAGE AND ADMINISTRATION

How to Use

Mix with half a cup of water 3-4 times per day. Ages 12 or older, 10 drops. Ages 12-2, 5 drops. Ages 2 and under, consult your Doctor.

Inactive:

Alcohol Base to Preserve Product

ACTIVE INGREDIENTS

Acid phos D100+100C 0.10mL each (EHPI), Arum tryph D100+100C 0.10mL each (HPUS), Balsamum peru D100+100C 0.10mL each (HPUS), Causticum D100+100C 0.10mL each (HPUS), Equisetum D100+100C 0.10mL each (HPUS), Glycerinum D100+100C 0.10mL each (HPUS), Helonias dio D70+70C 0.10mL each (HPUS)

Uses
Temporarily relieves discomfort associated with frequent urination, urinary tract issues, bladder problems, enlarged prostate, kidney problems, and elevated calcium levels.*

Uses
Temporarily relieves discomfort associated with frequent urination, urinary tract issues, bladder problems, enlarged prostate, kidney problems, and elevated calcium levels.*

KEEP OUT OF REACH OF CHILDREN

Warnings and Storage:

Ask a professional before use if pregnant or breastfeeding or if you have severe symptoms.

Keep away from children. If you have a reaction to this product that is not positive, discontinue use. Store in a cool and dry place

*CLAIMS BASED ON TRADITIONAL HOMEOPATHIC PRACTICE, NOT ACCEPTED MEDICAL EVIDENCE NOT FDA EVALUATED.
This product is not intended to diagnose, treat, cure, or prevent any disease.

Warnings and Storage:

Ask a professional before use if pregnant or breastfeeding or if you have severe symptoms.

Keep away from children. If you have a reaction to this product that is not positive, discontinue use. Store in a cool and dry place

*CLAIMS BASED ON TRADITIONAL HOMEOPATHIC PRACTICE, NOT ACCEPTED MEDICAL EVIDENCE NOT FDA EVALUATED.
This product is not intended to diagnose, treat, cure, or prevent any disease.

Entire package label